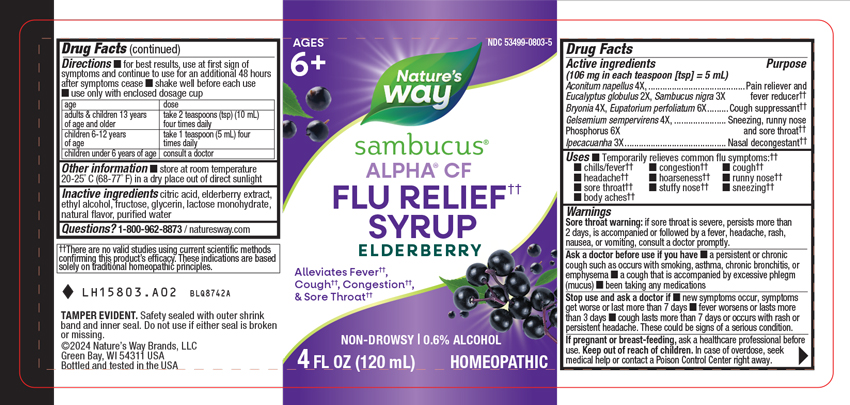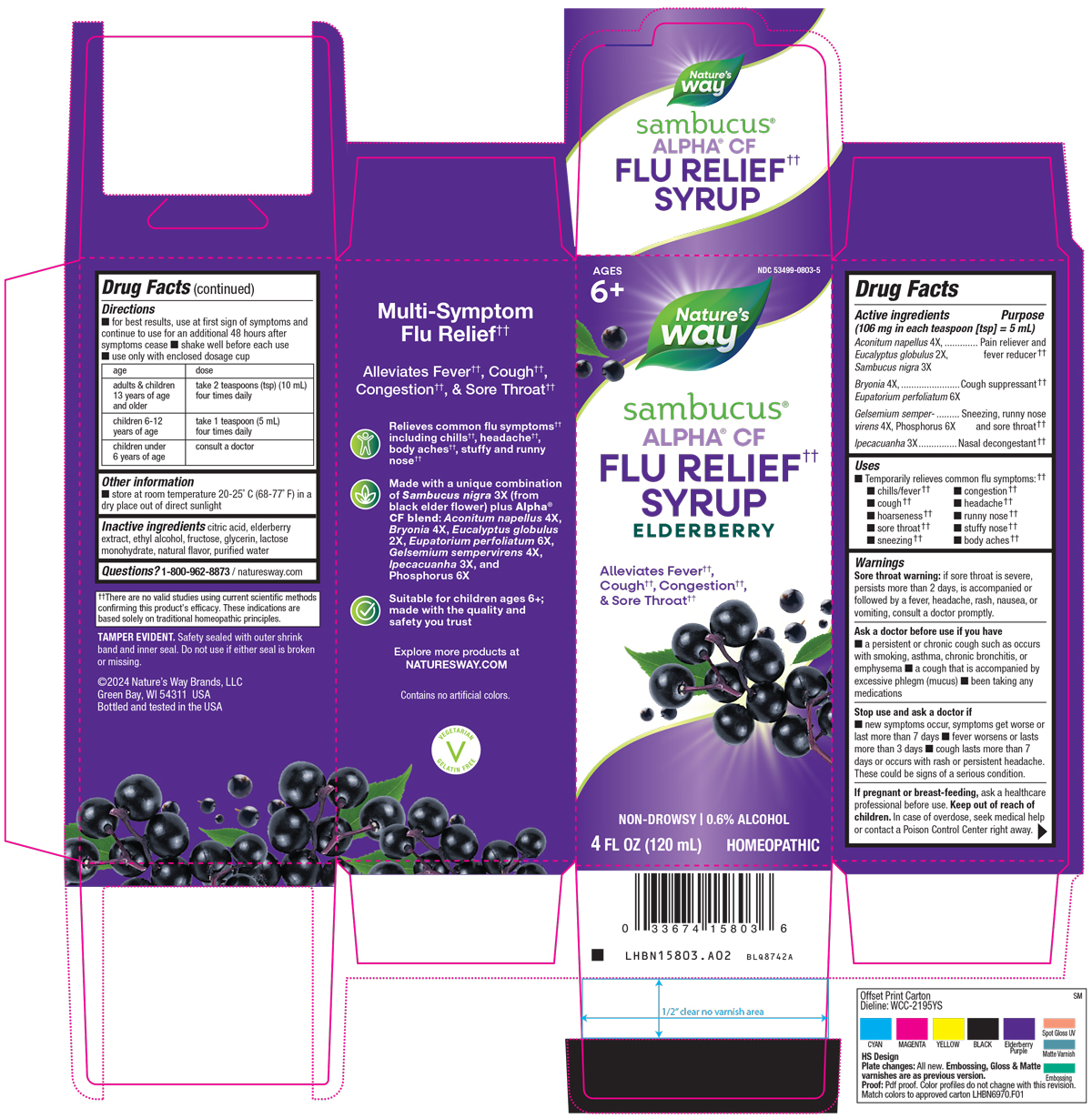 DRUG LABEL: Sambucus Flu Relief
NDC: 53499-0803 | Form: SYRUP
Manufacturer: Schwabe North America, Inc.
Category: homeopathic | Type: HUMAN OTC DRUG LABEL
Date: 20251208

ACTIVE INGREDIENTS: ACONITUM NAPELLUS 4 [hp_X]/120 mL; EUCALYPTUS GLOBULUS LEAF 2 [hp_X]/120 mL; SAMBUCUS NIGRA FLOWERING TOP 3 [hp_X]/120 mL; BRYONIA ALBA ROOT 4 [hp_X]/120 mL; EUPATORIUM PERFOLIATUM FLOWERING TOP 6 [hp_X]/120 mL; GELSEMIUM SEMPERVIRENS ROOT 4 [hp_X]/120 mL; PHOSPHORUS 6 [hp_X]/120 mL; IPECAC 3 [hp_X]/120 mL
INACTIVE INGREDIENTS: ANHYDROUS CITRIC ACID; EUROPEAN ELDERBERRY; ALCOHOL; FRUCTOSE; GLYCERIN; LACTOSE MONOHYDRATE; WATER

Sambucus Flu Relief

Active Ingredient

Aconitum napellus 4X

Eucalyptus globulus 2X

Sambucus nigra 3X

Bryonia 4X

Eupatorium perfoliatum 6X

Gelsemium sempervirens 4X

Phosphorus 6X

Ipecacuanha 3X

Inactive Ingredients

Citric Acid

Elderberry Extract

Ethyl Alcohol

Fructose

Glycerin

Lactose Monohydrate

Natural Flavor

Purified Water

Dosage & Administration

Directions:

For best results, use at first sign of symptoms and continue to use for an additonal 48 hours after symptoms cease.

Shake well before each use.

Use only with enclosed dosage cup.
Adults & children 13 years of age and older: Take 2 teaspoons (tsp) (10 mL) four times daily.

Children 6-12 years of age: Take 1 teaspoon (5 mL) four times daily.

Children under 6 years of age: Consult a doctor.

Indication & Usage

Temporarily relieves common flu symptoms: chills/ fever, congestion, cough, headache, hoarseness, runny nose, sore throat, stuffy nose, sneezing, and body aches.

Purpose

Temporarily relieves common flu symptoms: chills/ fever, congestion, cough, headache, hoarseness, runny nose, sore throat, stuffy nose, sneezing, and body aches.

Warnings

Sore throat warning: if sore throat is severe, persists more than 2 days, is accompanied or followed by a fever, headache, rash, nausea, or vomiting, consult a doctor promptly.

Ask Doctor

Ask a doctor before use if you have a persistent or chronic cough such as occurs with smoking, asthma, chronic bronchitis, or emphysema, a cough that is accompanied by excessive phlegm (mucus), been taking any medications.

Stop Use

Stop use and ask a doctor if new symptoms occur, symptoms get worse or last more than 7 days, fever worsens or lasts more than 3 days, cough lasts more than 7 days or occurs with rash or persistent headache.

These could be signs of a serious condition.

Pregnancy or Breast Feeding

If pregnant or breast-feeding, ask a healthcare professional before use.

Keep Out of Reach of Children

Overdose

In case of overdose, seek medical help or contact a Poison Control Center right away.